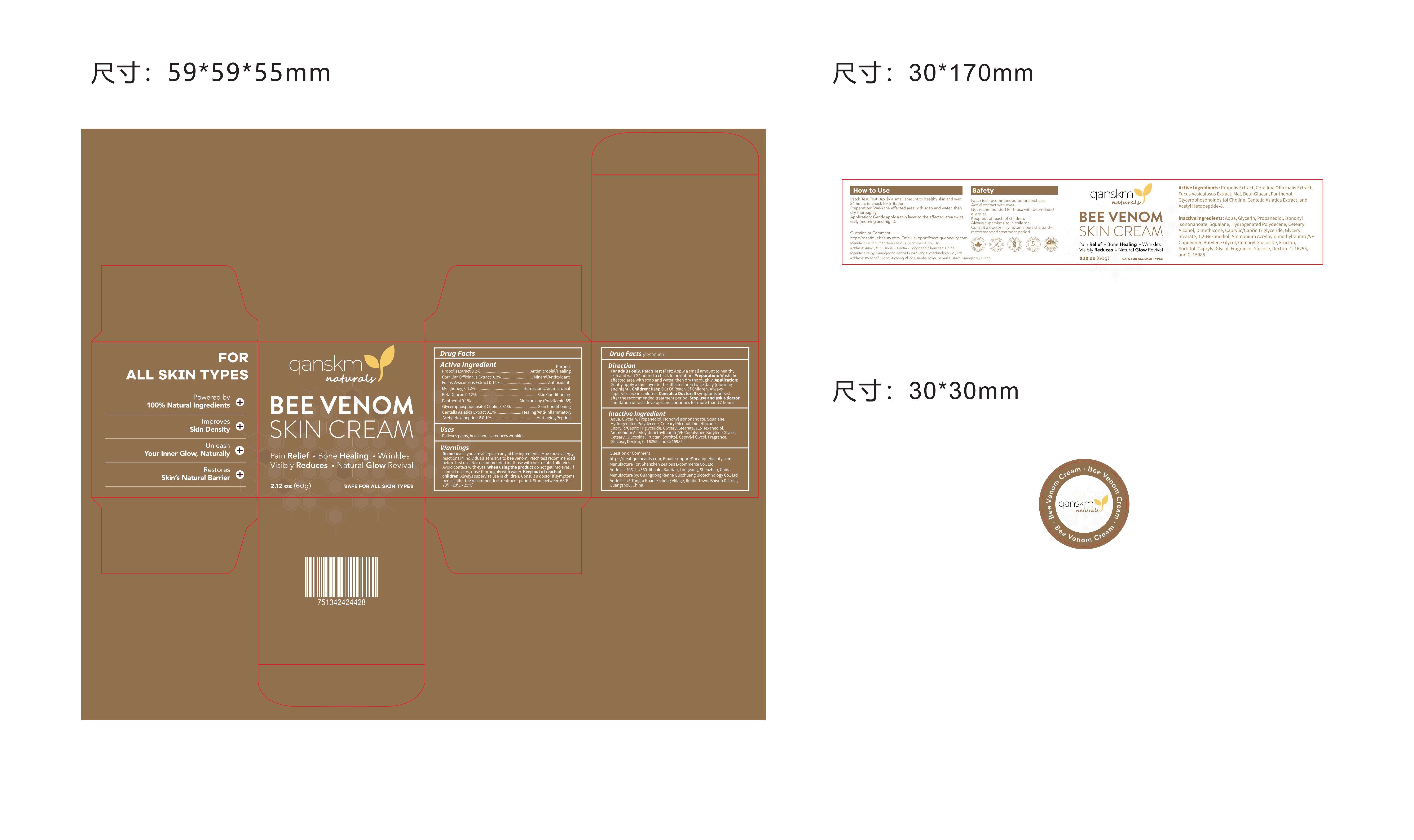 DRUG LABEL: Qanskm Bee Venom Skin Cream
NDC: 85587-002 | Form: CREAM
Manufacturer: Shenzhen Zealous Ecommerce Technology Co., Ltd
Category: otc | Type: HUMAN OTC DRUG LABEL
Date: 20250505

ACTIVE INGREDIENTS: FUCUS VESICULOSUS 0.15 g/100 g; GLYCEROPHOSPHOINOSITOL CHOLINE 0.1 g/100 g; CENTELLA ASIATICA TRITERPENOIDS 0.1 g/100 g; PROPOLIS CERA 0.2 g/100 g; TRANSFORMING GROWTH FACTOR BETA RECEPTOR TYPE 3 0.12 g/100 g; CORALLINA OFFICINALIS 0.2 g/100 g; PANTHENOL 0.1 g/100 g; MEL 0.12 g/100 g; ACETYL HEXAPEPTIDE-8 0.1 g/100 g
INACTIVE INGREDIENTS: AQUA; AMMONIUM ACRYLOYLDIMETHYLTAURATE/VP COPOLYMER; CAPRYLYL GLYCOL; FRAGRANCE 13576; DEXTRIN, CORN; BUTYLENE GLYCOL; SORBITOL; PROPANEDIOL; CETEARYL ALCOHOL; DIMETHICONE; CI 16255; GLYCERYL STEARATE; CETEARYL GLUCOSIDE; FRUCTOSE; ISONONYL ISONONANOATE; GLYCERIN; GLUCOSE; CI 15985; CAPRYLIC/CAPRIC TRIGLYCERIDE; SQUALANE; HYDROGENATED POLYDECENE TYPE I; 1,2-HEXANEDIOL

85587-002

Active Ingredient

PROPOLIS EXTRACT, CORALLINA OFFICINALIS EXTRACT, FUCUS VESICULOSUS EXTRACT, MEL (Honey), BETA-GLUCAN, PANTHENOL, GLYCEROPHOSPHOINOSITOL CHOLINE, CENTELLA ASIATICA EXTRACT, ACETYL HEXAPEPTIDE-8

Purpose

Pain Relief, Bone Healing, Wrinkles Reduces

Use

Use 1-2 time per day.

Warnings

Patch test recommended before first use. Avoid contact with eyes. Not recommended for those with bee-related allergies.

Do not use

Not recommended for those with bee-related allergies.

When Using

Patch test recommended before first use.

Stop Use

Stop use if symptoms persist after the recommended treatment period.

Ask Doctor

Consult a doctor if symptoms persist after the recommended treatment period.

Keep Out Of Reach Of Children

Directions

Apply a pea-sized amount to cleansed face and neck every morning and night.
Gently massage upward in circular motions.
Follow with SPF (daytime).

Inactive ingredients

AQUA, GLYCERIN, PROPANEDIOL, ISONONYL ISONONANOATE, SQUAL-ANE, HYDROGENATED POLYDECENE, CETEARYL ALCOHOL, DIMETHICONE, CAPRYLIC/CAPRIC TRIGLYCERIDE, GLYCERYL STEARATE 1,2-HEXANEDIOL, AMMONIUM ACRYLOYLDIMETHYLTAURATENP COPO. LYMER, BUTYLENE GLYCOL, CETEARYL GLUCOSIDE, FRUCTAN, PROPOLIS EXTRACT, SORBITOL, CAPRYLYL GLYCOL, FRAGRANCE, CORALLINA OFFI CINALIS EXTRACT, FUCUS VESICULOSUS EXTRACT, MEL, GLUCOSE, BETA-GLUCAN, PANTHENOL, GLYCEROPHOSPHOINOSITOL CHOLINE, DEXTRIN, CI 16255, CI 15985, CENTELLA ASIATICA EXTRACT, ACETYL HEXAPEPTIDE

Questions

Email: support@neatiquebeauty.com